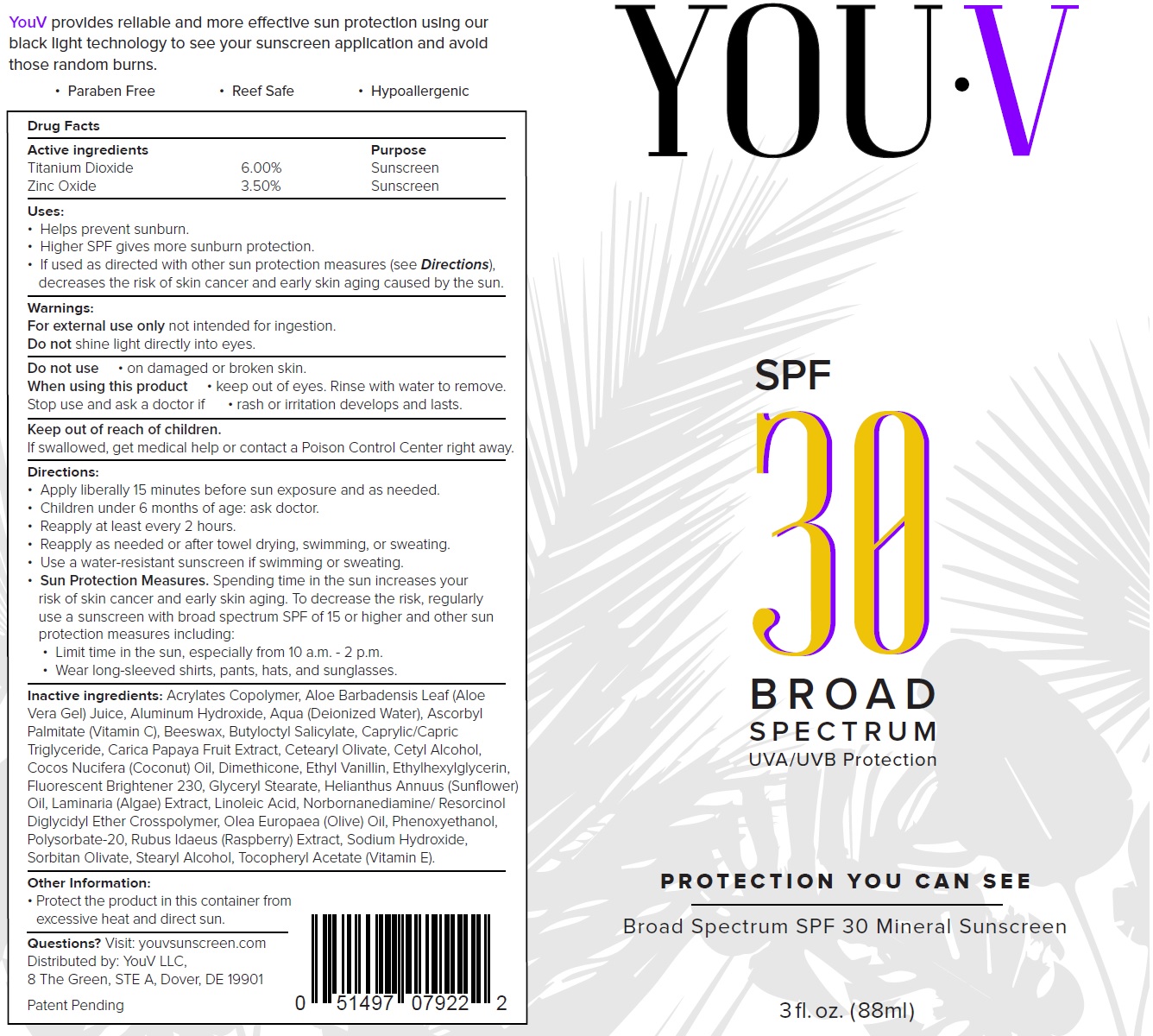 DRUG LABEL: YOU-V SPF-30 Broad Spectrum Sunscreen
NDC: 73243-045 | Form: LOTION
Manufacturer: YouV, LLC
Category: otc | Type: HUMAN OTC DRUG LABEL
Date: 20231111

ACTIVE INGREDIENTS: TITANIUM DIOXIDE 60 mg/1 mL; ZINC OXIDE 35 mg/1 mL
INACTIVE INGREDIENTS: ALOE VERA LEAF; ALUMINUM HYDROXIDE; WATER; ASCORBYL PALMITATE; YELLOW WAX; BUTYLOCTYL SALICYLATE; MEDIUM-CHAIN TRIGLYCERIDES; PAPAYA; CETEARYL OLIVATE; CETYL ALCOHOL; COCONUT OIL; DIMETHICONE; ETHYL VANILLIN; ETHYLHEXYLGLYCERIN; GLYCERYL MONOSTEARATE; HELIANTHUS ANNUUS FLOWERING TOP; LINOLEIC ACID; GREEN OLIVE; PHENOXYETHANOL; POLYSORBATE 20; RASPBERRY; SODIUM HYDROXIDE; SORBITAN OLIVATE; STEARYL ALCOHOL; .ALPHA.-TOCOPHEROL ACETATE

YOU-V SPF-30 Broad Spectrum Sunscreen Lotion

Active ingredients

Titanium Dioxide 6.00%

Zinc Oxide 3.50%

Purpose

Sunscreen

Uses:

- Helps prevent sunburn.
- Higher SPF gives more sunburn protection.
- If used as directed with other sun protection measures (see), Decreases the risk of skin cancer and early skin aging caused by the sun. Directions

Warnings:

not intended for ingestion. For external use only.

shine light directly into eyes. Do not

Do not use

- on damaged or broken skin.

When using this product

- keep out of eyes. Rinse with water to remove.

Stop use and ask a doctor if

- rash or irritation develops and lasts.

Keep out of reach of children.

If swallowed, get medical help or contact a Poison Control Center right away.

Directions:

- Apply liberally 15 minutes before sun exposure and as needed.
- Children under 6 months of age: ask doctor
- Reapply at least every 2 hours.
- Reapply as needed or after towel drying, swimming, or sweating.
- Use a water-resistant sunscreen if swimming or sweating.
- Spending time in the sun increases your risk of skin cancer and early skin aging. To decrease the risk, regularly use a sunscreen with broad spectrum SPF of 15 or higher and other sun protection measures including: Sun Protection Measures:
- Limit time in the sun, especially between 10am and 2pm.
- Wear long-sleeved shirts, pants, hats, and sunglasses.

Other ingredients:

Acrylates Copolymer, Aloe Barbadensis Leaf (Aloe Vera Gel) Juice, Aluminum Hydroxide, Aqua (Deionized Water), Ascorbyl Palmitate (Vitamin C), Beeswax, Butyloctyl Salicylate, Caprylic/Capric Triglyceride, Carica Papaya Fruit Extract, Cetearyl Olivate, Cetyl Alcohol, Cocos Nucifera (Coconut) Oil, Dimethicone, Ethyl Vanillin, Ethylhexylglycerin, Fluorescent Brightener 230, Glyceryl Stearate, Helianthus Annuus (Sunflower) Oil, Laminaria (Algae) Extract, Linoleic Acid, Norbornanediamine/ Resorcinol Diglycidyl Ether Crosspolymer, Olea Europaea (Olive) Oil, Phenoxyethanol, Polysorbate-20, Rubus Idaeus (Raspberry) Extract, Sodium Hydroxide, Sorbitan Olivate, Stearyl Alcohol, Tocopheryl Acetate (Vitamin E).

Other Information:

- Protect the product in this container from excessive heat and direct sun.

Questions?

Visit: youvsunscreen.com Distributed by: YouV LLC,